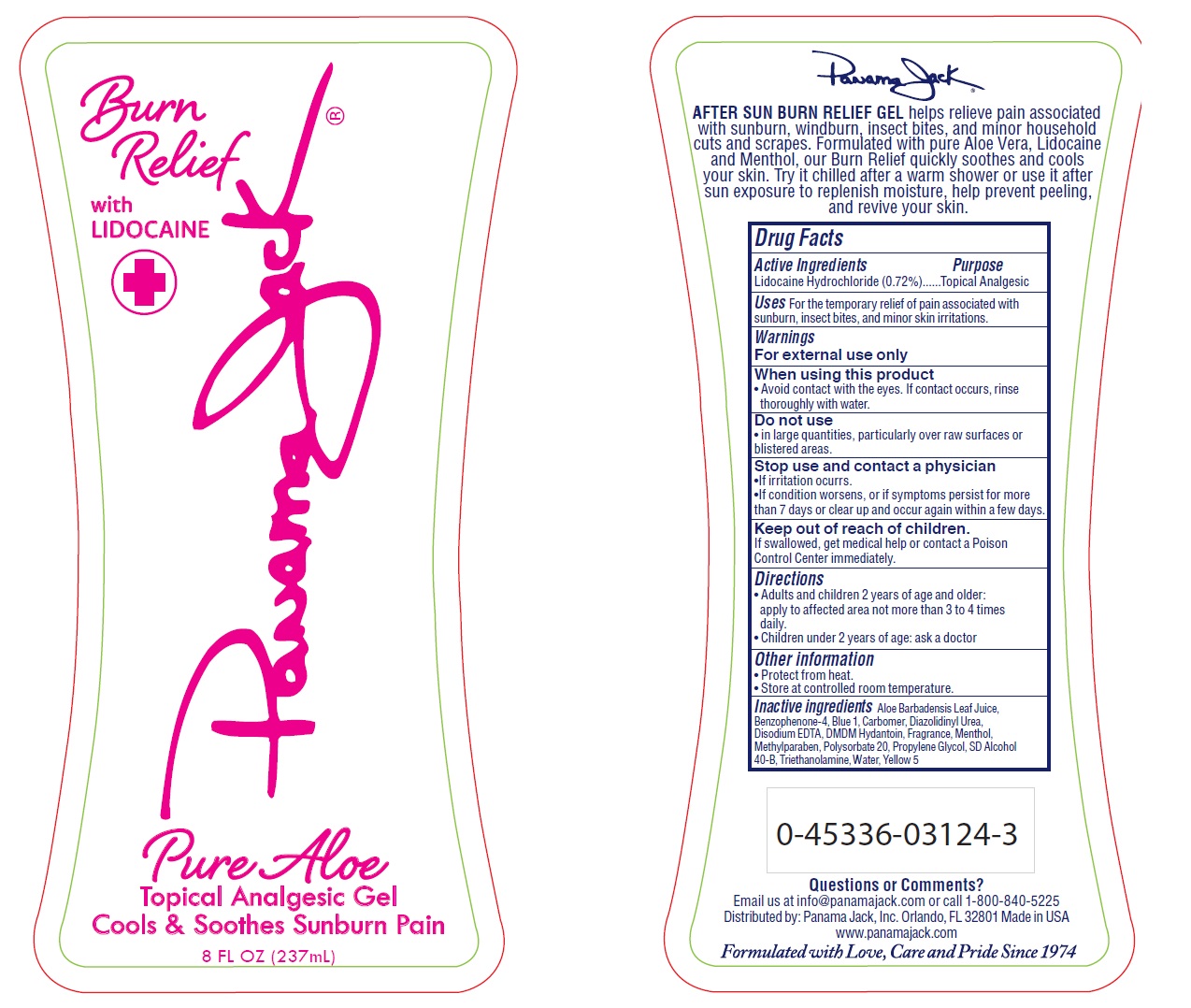 DRUG LABEL: Panama Jack
NDC: 58443-0204 | Form: GEL
Manufacturer: Prime Enterprises Inc.
Category: otc | Type: HUMAN OTC DRUG LABEL
Date: 20200117

ACTIVE INGREDIENTS: LIDOCAINE HYDROCHLORIDE 7.13 mg/1 mL
INACTIVE INGREDIENTS: ALOE VERA LEAF; SULISOBENZONE; DIAZOLIDINYL UREA; EDETATE DISODIUM; MENTHOL; METHYLPARABEN; TROLAMINE; CARBOMER HOMOPOLYMER TYPE C (ALLYL PENTAERYTHRITOL CROSSLINKED); ALCOHOL; WATER; POLYSORBATE 20; PROPYLENE GLYCOL; DMDM HYDANTOIN

Panama Jack Burn Relief with Lidocaine

Active Ingredients

Lidocaine Hydrochloride (0.72%)

Purpose

Topical Analgesic

Uses

For the temporary relief of pain associated with sunburn, insect bites, and minor skin irritations.

WARNINGS

For external use only.

When using this product

- Avoid contact with the eyes. If contact occurs, rinse thoroughly with water.

Do not use

- in large quantities, particularly over raw surfaces or blistered areas.

Stop use and contact a physician

- If irritation occurs.
- If condition worsens, or if symptoms persist for more than 7 days or clear up and occur again within a few days.

Keep out of reach of children.

If swallowed, get medical help or contact a Poison Control Center immediately.

Directions

- Adults and children 2 years of age and older: apply to affected area not more than 3 to 4 times daily.
- Children under 2 years of age: ask a doctor

Other Information

- Protect from heat,
- Store at controlled room temperature.

INACTIVE INGREDIENT

Aloe Barbadensis Leaf Juice, Benzophenone-4, Blue 1, Carbomer, Diazolidinyl Urea, Disodium EDTA, DMDM Hydantoin, Fragrance, Menthol, Methylparaben, Polysorbate 20, Propylene Glycol, SD Alcohol 40-B, Triethanolamine, Water, Yellow 5

Questions or Comments?

Email us at info@panamajack.com or call 1-800-840-5225